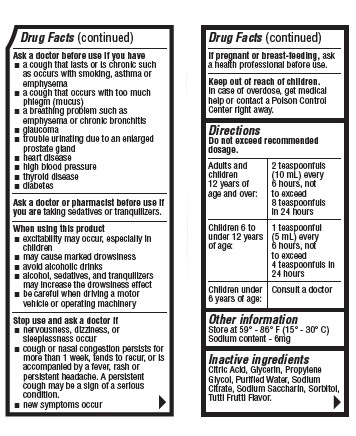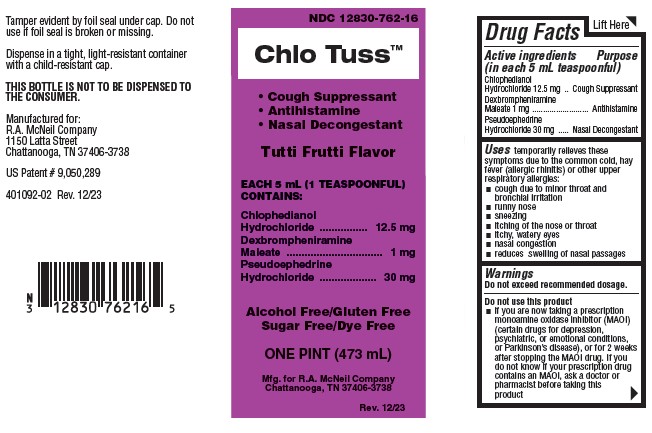 DRUG LABEL: Chlo Tuss
NDC: 12830-762 | Form: LIQUID
Manufacturer: R.A. McNeil Company
Category: otc | Type: HUMAN OTC DRUG LABEL
Date: 20251015

ACTIVE INGREDIENTS: CHLOPHEDIANOL HYDROCHLORIDE 12.5 mg/5 mL; DEXBROMPHENIRAMINE MALEATE 1 mg/5 mL; PSEUDOEPHEDRINE HYDROCHLORIDE 30 mg/5 mL
INACTIVE INGREDIENTS: CITRIC ACID MONOHYDRATE; GLYCERIN; PROPYLENE GLYCOL; WATER; SODIUM CITRATE; SACCHARIN SODIUM; SORBITOL

Chlo Tuss

Drug Facts

Active ingredients

(in each 5 mL teaspoonful)

Chlophedianol Hydrochloride 12.5 mg

Dexbrompheniramine Maleate 1 mg

Pseudoephedrine Hydrochloride 30 mg

Purpose

Cough Suppressant

Antihistamine

Nasal Decongestant

Uses

temporarily relieves these symptoms due to the common cold, hay fever (allergic rhinitis) or other upper respiratory allergies:

- cough due to minor throat and bronchial irritation
- runny nose
- sneezing
- itching of the nose or throat
- itchy, watery eyes
- nasal congestion
- reduces swelling of nasal passages

Warnings

Do not exceed recommended dosage.

Do not use this product

- if you are now taking a prescription monoamine oxidase inhibitor (MAOI) (certain drugs for depression, psychiatric, or emotional conditions, or Parkinson's disease), or for 2 weeks after stopping the MAOI drug. If you do not know if your prescription drug contains an MAOI, ask a doctor or pharmacist before taking this product

Ask a doctor before use if you have

- a cough that lasts or is chronic such as occurs with smoking, asthma or emphysema
- a cough that occurs with too much phlegm (mucus)
- a breathing problem such as emphysema or chronic bronchitis
- glaucoma
- trouble urinating due to an enlarged prostate gland
- heart disease
- high blood pressure
- thyroid disease
- diabetes

Ask a doctor or pharmacist before use if you are

taking sedatives or tranquilizers.

When using this product

- excitability may occur, especially in children
- may cause marked drowsiness
- avoid alcoholic drinks
- alcohol, sedatives, and tranquilizers may increase the drowsiness effect
- be careful when driving a motor vehicle or operating machinery

Stop use and ask a doctor if

- nervousness, dizziness, or sleeplessness occur
- cough or nasal congestion persists for more than 1 week, tends to recur, or is accompanied by a fever, rash or persistent headache. A persistent cough may be a sign of a serious condition.
- new symptoms occur

If pregnant or breast-feeding,

ask a health professional before use.

Keep out of reach of children.

In case of overdose, get medical help or contact a Poison Control Center right away.

Directions

Do not exceed recommended dosage.

Adults and children 12 years of age and over: | 2 teaspoonfuls (10 mL); every 6 hours, not to; exceed 8 teaspoonfuls; in 24 hours
Children 6 to under 12 years of age: | 1 teaspoonful (5 mL); every 6 hours, not to; exceed 4 teaspoonfuls; in 24 hours
Children under 6 years of age: | Consult a doctor

Other information

Store at 59° - 86°F (15° - 30°C)

Inactive ingredients

Citric Acid, Glycerin, Propylene Glycol, Purified Water, Sodium Citrate, Sodium Saccharin, Sorbitol, Tutti Frutti Flavor.

Questions? Comments?

Serious side effects associated with use of this product may be reported to this number. Call 1-423-493-9170
(8 a.m. to 5 p.m.)